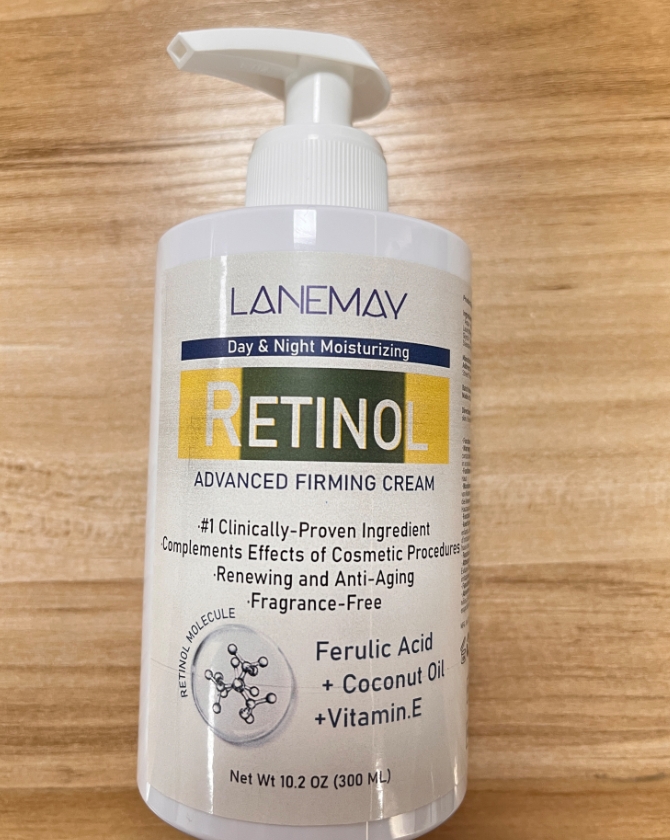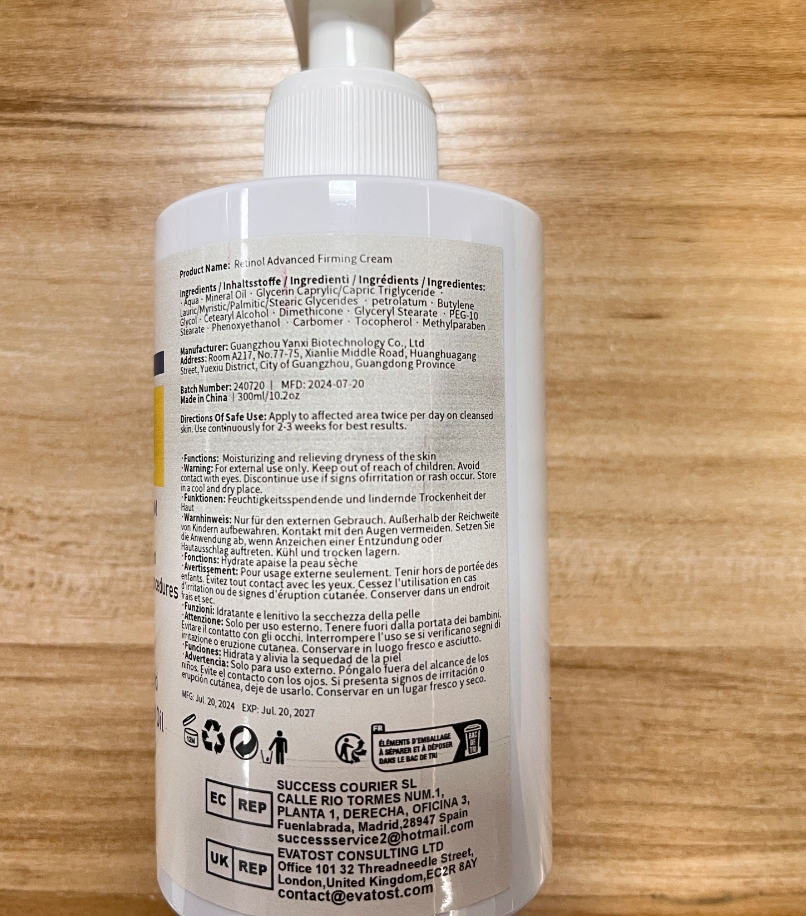 DRUG LABEL: Retinol Advanced Firming Cream
NDC: 84025-086 | Form: CREAM
Manufacturer: Guangzhou Yanxi Biotechnology Co., Ltd
Category: otc | Type: HUMAN OTC DRUG LABEL
Date: 20240724

ACTIVE INGREDIENTS: MINERAL OIL 5 mg/100 mL; PHENOXYETHANOL 3 mg/100 mL
INACTIVE INGREDIENTS: WATER

DOSAGE AND ADMINISTRATION

USE AS A NORMAL FACE CREAM

WARNINGS

keep out of children

INACTIVE INGREDIENT

Aqua

INDICATIONS AND USAGE

For Dry Skin

keep out of children

PURPOSE

Moisturizing and relieving dryness of the skin